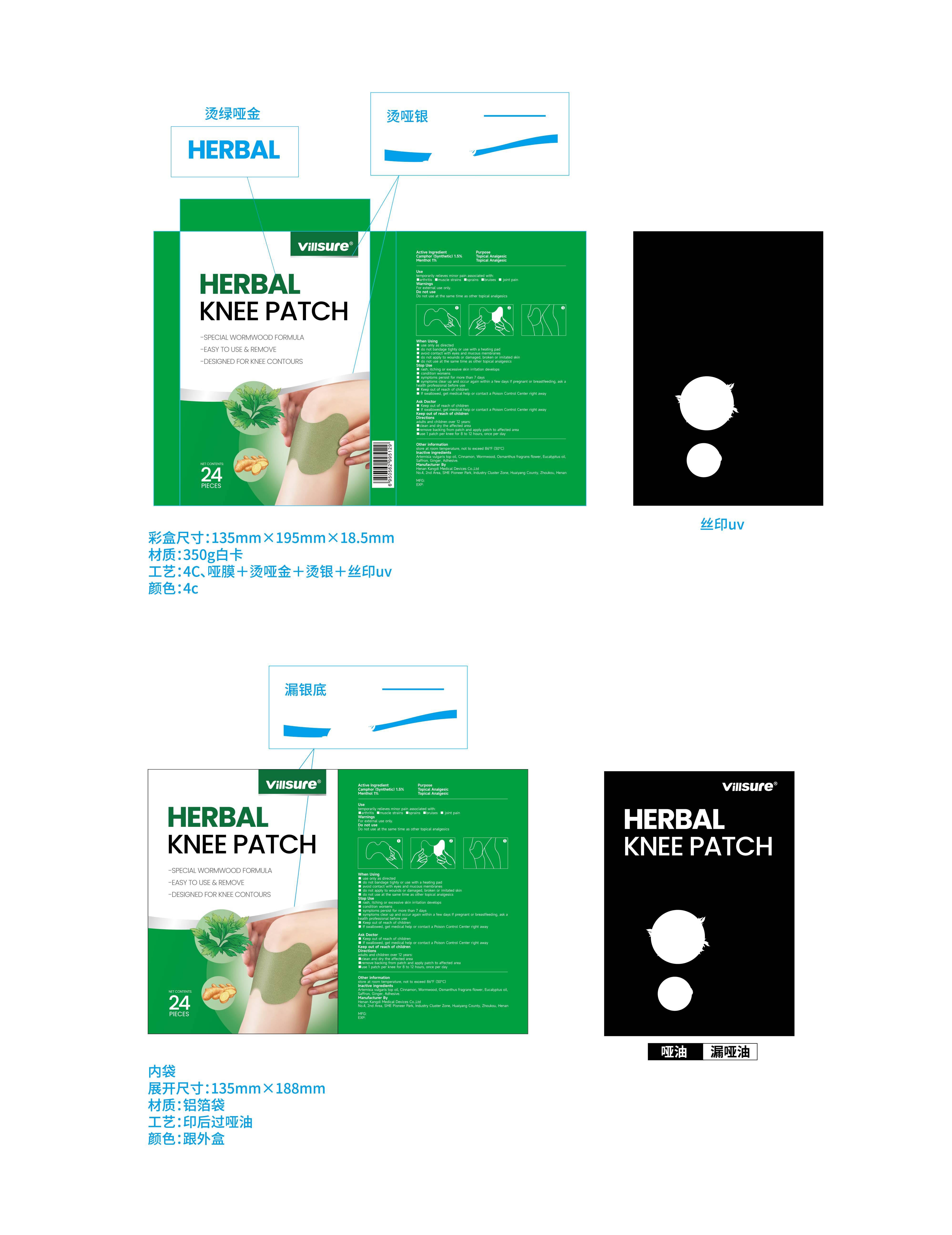 DRUG LABEL: Herbal Knee Patch
NDC: 69561-006 | Form: PATCH
Manufacturer: Henan Kangdi Medical Devices Co., Ltd
Category: otc | Type: HUMAN OTC DRUG LABEL
Date: 20260207

ACTIVE INGREDIENTS: MENTHOL 1 g/100 1; CAMPHOR (SYNTHETIC) 1.5 g/100 1
INACTIVE INGREDIENTS: ARTEMISIA VULGARIS TOP OIL; CINNAMON; EUCALYPTUS OIL; GINGER; OSMANTHUS FRAGRANS FLOWER; WORMWOOD; DIETHYLENE GLYCOL ABIETATE; SAFFRON

69561-006

Active Ingredient

Camphor(SYNTHETIC) 1.5%
Menthol 1%

Purpose

Topical Analgesic

Use

temporarily relieves minor pain associated with:
■arthritis

■muscle strains

■sprains

■bruises

■ joint pain

Warnings

For external use only.

Do not use at the same time as other topical analgesics

When Using

■ use only as directed
■ do not bandage tighty or use with a heating pad
■ avoid contact with eyes and mucous membranes
■ do not apply to wounds or damaged, broken or imitated skin
■ do not use at the same time as other topical analgesics

Stop Use

■ rash, itching or excessive skin irritation develops
■ condition worsens
■ symptoms persist for more than 7 days
■ symptoms clear up and occur again within a few days If pregnant or breastfeeding, ask a health professional before use
■ Keep out of reach of children
■ If swallowed, get medical help or contact a Poison Control Center right away

Ask Doctor

■ Keep out of reach of children
■ If swallowed, get medical help or contact a Poison Control Center right away

Keep Oot Of Reach Of Children

Keep out of reach of children

Directions

adults and children over 12 years:
■clean and dry the affected area
■remove backing from patch and apply patch to affected area
■use 1 patch per knee for 8 to 12 hours, once per day

Other information

store at room temperature, not to exceed 86°F (30°C)

Inactive ingredients

Artemisia vulgaris top oil, Cinnamon, Wormwood, Osmanthus fragrans flower, Eucalyptus oil, Saffron, Ginger,Adhesive